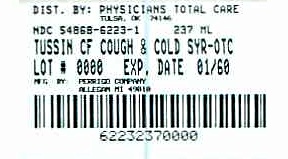 DRUG LABEL: Tussin CF
NDC: 54868-6223 | Form: LIQUID
Manufacturer: Physicians Total Care, Inc.
Category: otc | Type: HUMAN OTC DRUG LABEL
Date: 20090630

ACTIVE INGREDIENTS: DEXTROMETHORPHAN HYDROBROMIDE 10 mg/5 mL; GUAIFENESIN 100 mg/5 mL; PHENYLEPHRINE HYDROCHLORIDE 5 mg/5 mL
INACTIVE INGREDIENTS: ANHYDROUS CITRIC ACID; EDETATE DISODIUM; FD&C RED NO. 40; GLYCERIN; PROPYLENE GLYCOL; WATER; SODIUM BENZOATE; SODIUM CITRATE; SORBITOL; SUCRALOSE

Tussin CF Drug Data

Active ingredient (in each 5 mL tsp)

Dextromethorphan HBr, USP 10 mg

Guaifenesin, USP 100 mg

Phenylephrine HCl, USP 5 mg

Purpose

Cough suppressant

Expectorant

Nasal decongestant

Uses

- helps loosen phlegm (mucus) and thin bronchial secretions to drain bronchial tubes
- temporarily relieves these symptoms occurring with a cold:
- nasal congestion
- cough due to minor throat and bronchial irritation

Warnings

Do not use

- if you are now taking a prescription monoamine oxidase inhibitor (MAOI) (certain drugs for depression, psychiatric, or emotional conditions, or Parkinson's disease), or for 2 weeks after stopping the MAOI drug. If you do not know if your prescription drug contains an MAOI, ask a doctor or pharmacist before taking this product.

Ask a doctor before use if you have

- heart disease
- high blood pressure
- thyroid disease
- diabetes
- trouble urinating due to an enlarged prostate gland
- cough that occurs with too much phlegm (mucus)
- cough that lasts or is chronic such as occurs with smoking, asthma, chronic bronchitis or emphysema

When using this product

do not use more than directed

Stop use and ask a doctor if

- you get nervous, dizzy, or sleepless
- symptoms do not get better within 7 days or are accompanied by fever
- cough lasts more than 7 days, comes back, or is accompanied by fever, rash, or persistent headache. These could be signs of a serious condition.

If pregnant or breast-feeding,

ask a health professional before use.

Keep out of reach of children.

In case of overdose, get medical help or contact a Poison Control Center right away. (1-800-222-1222)

Directions

- do not take more than 6 doses in any 24-hour period
- this adult product is not intended for use in children under 12 years of age
- mL = milliliter; tsp = teaspoonful

age | dose
adults and children 12 years and over | 10 mL (2 tsp) every 4 hours
children under 12 years | do not use

Other information

- each teaspoon contains: sodium 3 mg
- store at 20º-25ºC (68º-77ºF)

Inactive ingredients

anhydrous citric acid, edetate disodium, FD&C red no. 40, flavor, glycerin, propylene glycol, purified water, sodium benzoate, sodium citrate, sorbitol solution, sucralose

Questions or comments?

1-800-719-9260

Additional barcode labeling by:
Physicians Total Care, Inc.
Tulsa, OK 74146

Principal Display Panel

Non-Drowsy

Tussin CF Cough & Cold

Cough Suppressant

(Dextromethorphan HBr) Expectorant (Guaifenesin)

Nasal Decongestant

(Phenylephrine HCl)

Relieves: Coughs /Stuffy Nose /Chest Congestion Mucus

Adult

For Ages 12 & Over

Alcohol Free

Compare to active ingredients of Robitussin® Cough & Cold CF

NDC 54868-6223-1

237 mL